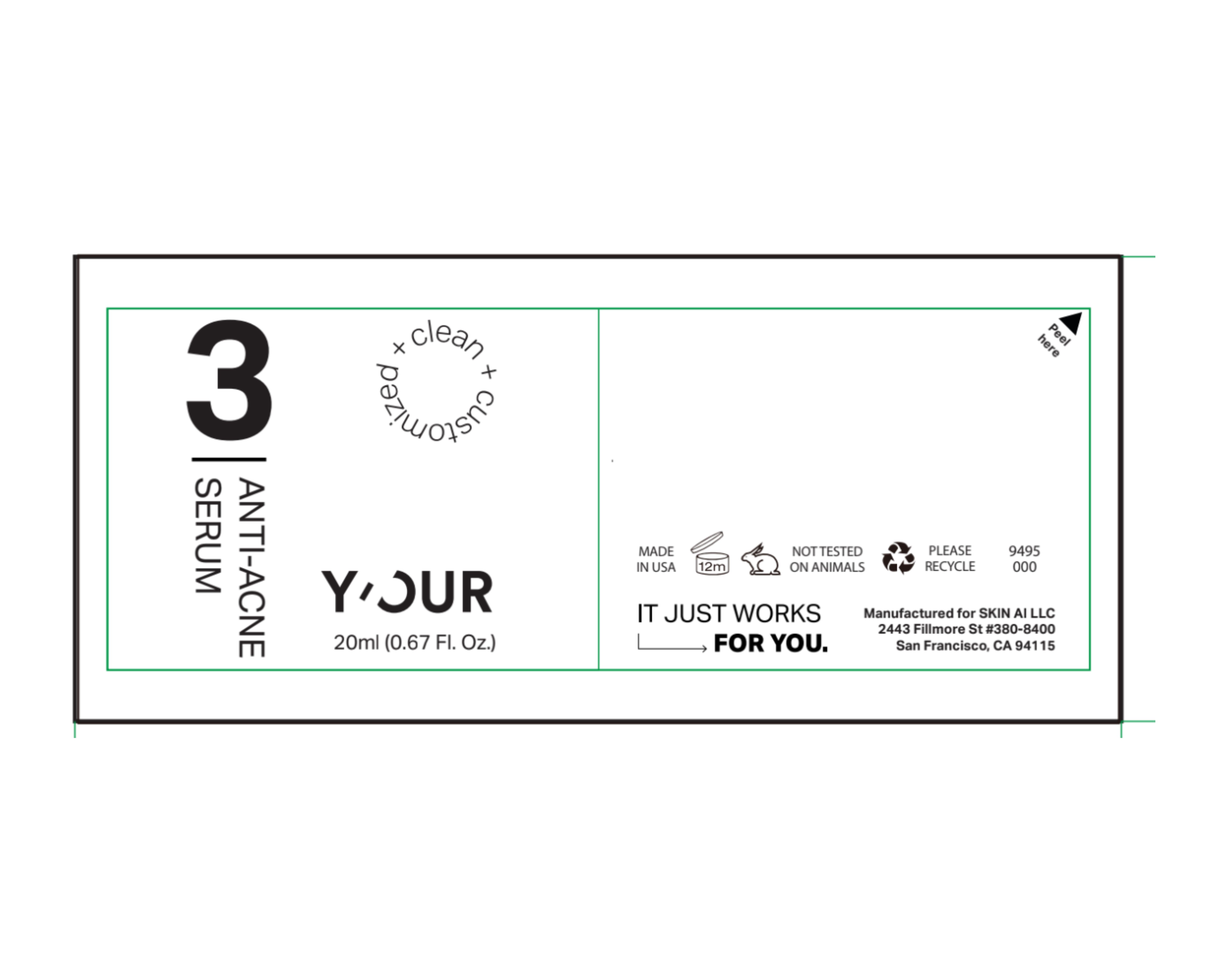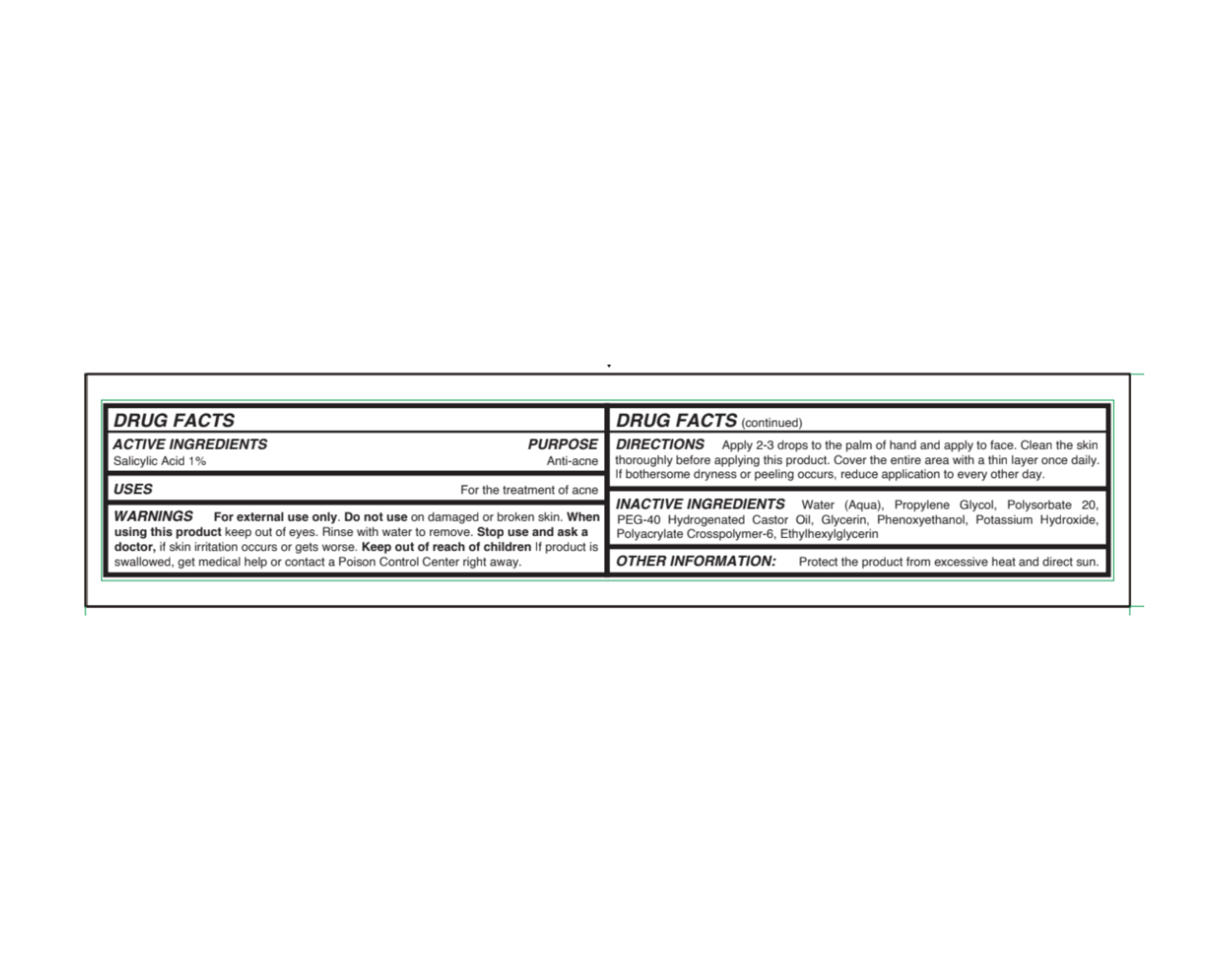 DRUG LABEL: YOUR ANTI-ACNE SERUM
NDC: 84229-2101 | Form: LIQUID
Manufacturer: Skin Ai, LLC
Category: otc | Type: HUMAN OTC DRUG LABEL
Date: 20251013

ACTIVE INGREDIENTS: SALICYLIC ACID 0.2 g/20 mL
INACTIVE INGREDIENTS: PROPYLENE GLYCOL; POLYSORBATE 20; PHENOXYETHANOL; POLYACRYLATE CROSSPOLYMER-6; GLYCERIN; PEG-40 HYDROGENATED CASTOR OIL; POTASSIUM HYDROXIDE; WATER; ETHYLHEXYLGLYCERIN

ACTIVE INGREDIENT

Salicylic Acid 1%

INDICATIONS AND USAGE

For the treatment of acne

WARNINGS

For external use only. Do not use on damaged or broken skin. Whenusing this product keep out of eyes. Rinse with water to remove. Stop use and ask a doctor, if skin irritation occurs or gets worse.

Keep out of reach of children If product is swallowed, get medical help or contact a Poison Control Center right away.

DOSAGE AND ADMINISTRATION

Apply 2-3 drops to the palm of hand and apply to face. Clean the skin thoroughly before applying this product. Cover the entire area with a thin layer once daily. If bothersome dryness or peeling occurs, reduce application to every other day.

INACTIVE INGREDIENT

Water (Aqua), Propylene Glycol, Polysorbate 20,
PEG-40 Hydrogenated Castor Oil, Glycerin, Phenoxyethanol, Potassium Hydroxide,
Polyacrylate Crosspolymer-6, Ethylhexylglycerin

OTHER SAFETY INFORMATION

Protect the product from excessive heat and direct sun.

PURPOSE

Anti-acne

PACKAGE LABEL

Y'OUR

ANTI-ACNE SERUM

20ml (0.67 Fl. Oz.)

MADE IN USA

NOT TESTED ON ANIMALS

PLEASE RECYCLE